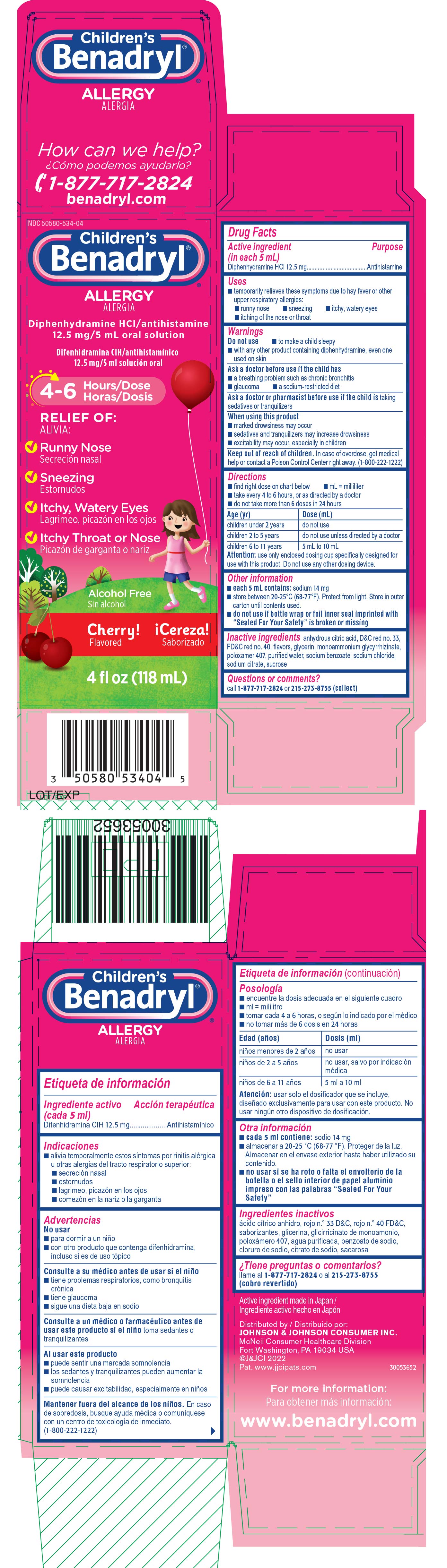 DRUG LABEL: Childrens Benadryl ALLERGY
NDC: 50580-534 | Form: SOLUTION
Manufacturer: Kenvue Brands LLC
Category: otc | Type: HUMAN OTC DRUG LABEL
Date: 20250513

ACTIVE INGREDIENTS: DIPHENHYDRAMINE HYDROCHLORIDE 12.5 mg/5 mL
INACTIVE INGREDIENTS: ANHYDROUS CITRIC ACID; D&C RED NO. 33; FD&C RED NO. 40; GLYCERIN; AMMONIUM GLYCYRRHIZATE; POLOXAMER 407; WATER; SODIUM BENZOATE; SODIUM CHLORIDE; SODIUM CITRATE, UNSPECIFIED FORM; SUCROSE

Children's Benadryl® ALLERGY

Drug Facts

Active ingredient (in each 5 mL)

Diphenhydramine HCl 12.5 mg

Purpose

Antihistamine

Uses

- temporarily relieves these symptoms due to hay fever or other upper respiratory allergies:
  - runny nose
  - sneezing
  - itchy, watery eyes
  - itching of the nose or throat

Warnings

Do not use

- to make a child sleepy
- with any other product containing diphenhydramine, even one used on skin

Ask a doctor before use if the child has

- a breathing problem such as chronic bronchitis
- glaucoma
- a sodium-restricted diet

Ask a doctor or pharmacist before use if the child is taking sedatives or tranquilizers

When using this product

- marked drowsiness may occur
- sedatives and tranquilizers may increase drowsiness
- excitability may occur, especially in children

Keep out of reach of children. In case of overdose, get medical help or contact a Poison Control Center right away. (1-800-222-1222)

Directions

- find right dose on chart below
- mL = milliliter
- take every 4 to 6 hours, or as directed by a doctor
- do not take more than 6 doses in 24 hours

Age (yr) | Dose (mL)
children under 2 years | do not use
children 2 to 5 years | do not use unless directed by a doctor
children 6 to 11 years | 5 mL to 10 mL

Attention: use only enclosed dosing cup specifically designed for use with this product. Do not use any other dosing device.

Other information

- each 5 mL contains: sodium 14 mg
- store between 20-25°C (68-77°F). Protect from light. Store in outer carton until contents used.
- do not use if bottle wrap or foil inner seal imprinted with “Sealed For Your Safety” is broken or missing

Inactive ingredients

anhydrous citric acid, D&C red no. 33, FD&C red no. 40, flavors, glycerin, monoammonium glycyrrhizinate, poloxamer 407, purified water, sodium benzoate, sodium chloride, sodium citrate, sucrose

Questions or comments?

call 1-877-717-2824 or 215-273-8755 (collect)

PRINCIPAL DISPLAY PANEL

NDC 50580-534-04

Children's
Benadryl®

ALLERGY

Diphenhydramine HCl/antihistamine
12.5 mg/5 mL oral solution

4-6 Hours/Dose

RELIEF OF:

- Runny Nose
- Sneezing
- Itchy, Watery Eyes
- Itchy Throat or Nose

Alcohol Free

Cherry!
Flavored

4 fl oz (118 mL)